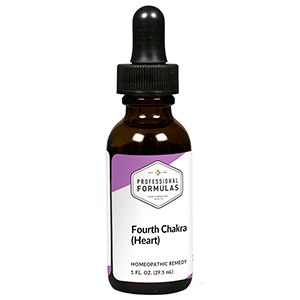 DRUG LABEL: Fourth Chakra (Heart)
NDC: 63083-7304 | Form: LIQUID
Manufacturer: Professional Complementary Health Formulas
Category: homeopathic | Type: HUMAN OTC DRUG LABEL
Date: 20190815

ACTIVE INGREDIENTS: AMARYLLIS BELLADONNA WHOLE 8 [hp_X]/29.5 mL; CALCIUM SULFATE ANHYDROUS 8 [hp_X]/29.5 mL; POTASSIUM SULFATE 8 [hp_X]/29.5 mL; WOOD CREOSOTE 8 [hp_X]/29.5 mL; SODIUM SULFATE 8 [hp_X]/29.5 mL; ARANEUS DIADEMATUS 12 [hp_X]/29.5 mL; COLCHICUM AUTUMNALE BULB 12 [hp_X]/29.5 mL; FORMICA RUFA 12 [hp_X]/29.5 mL; NAJA NAJA VENOM 12 [hp_X]/29.5 mL; SILICON DIOXIDE 30 [hp_X]/29.5 mL; MALACHITE GREEN 30 [hp_X]/29.5 mL
INACTIVE INGREDIENTS: ALCOHOL; WATER

RCT4

ACTIVE INGREDIENTS

Belladonna 8X
Calcarea sulphurica 8X
Kali sulphuricum 8X
Kreosotum 8X
Natrum sulphuricum 8X
Aranea diadema 12X
Colchicum autumnale 12X
Formica rufa 12X
Naja tripudians 12X
Chrysoprase 30X, 60X, 100X
Malachite 30X, 60X, 100X

QUESTIONS

Professional Formulas

PO Box 2034 Lake Oswego, OR 97035

INDICATIONS

Temporarily relieves wanting to withdraw from social interaction, being overcritical or demanding of others and self, apathy, isolation, desire to fill the needs of others at the cost of own balance, or victimhood.*

PURPOSE

*Claims based on traditional homeopathic practice, not accepted medical evidence. Not FDA evaluated.

WARNINGS

In case of overdose, get medical help or contact a poison control center right away.

Keep out of the reach of children.

PREGNANCY OR BREAST FEEDING

If pregnant or breastfeeding, ask a healthcare professional before use.

DIRECTIONS

Place drops under tongue 30 minutes before/after meals. Adults and children 12 years and over: Take 5 drops up to 4 times per day for up to one month. Consult a physician for use in children under 12 years of age.

OTHER INFORMATION

Tamper resistant. If seal is broken, do not use. After opening, close container tightly and store at room temperature away from heat.

INACTIVE INGREDIENTS

20% ethanol, purified water.

LABEL

Est 1985

Professional Formulas

Complementary Health

Fourth Chakra (Heart)

Homeopathic Remedy

1 FL. OZ. (29.5 mL)